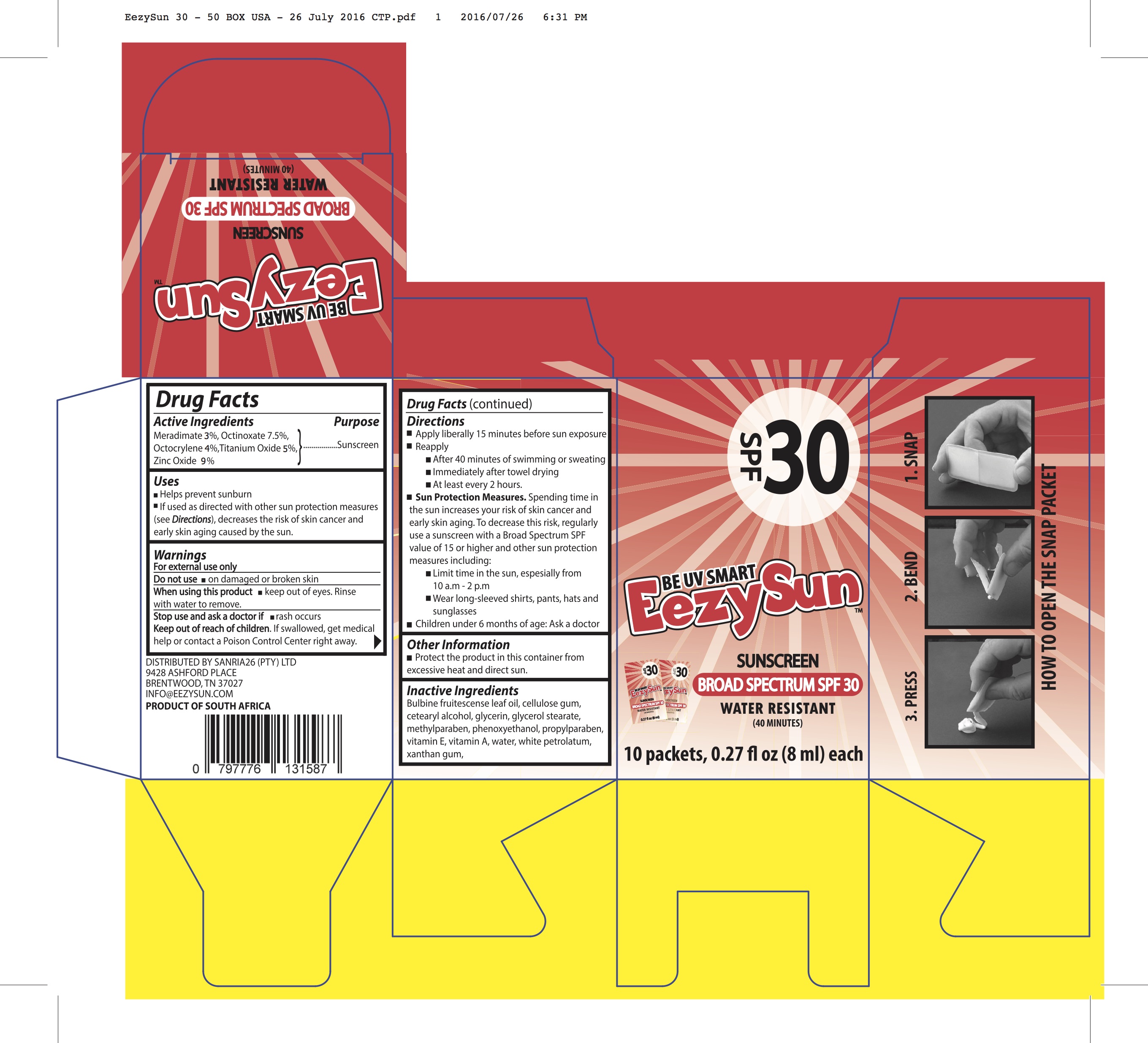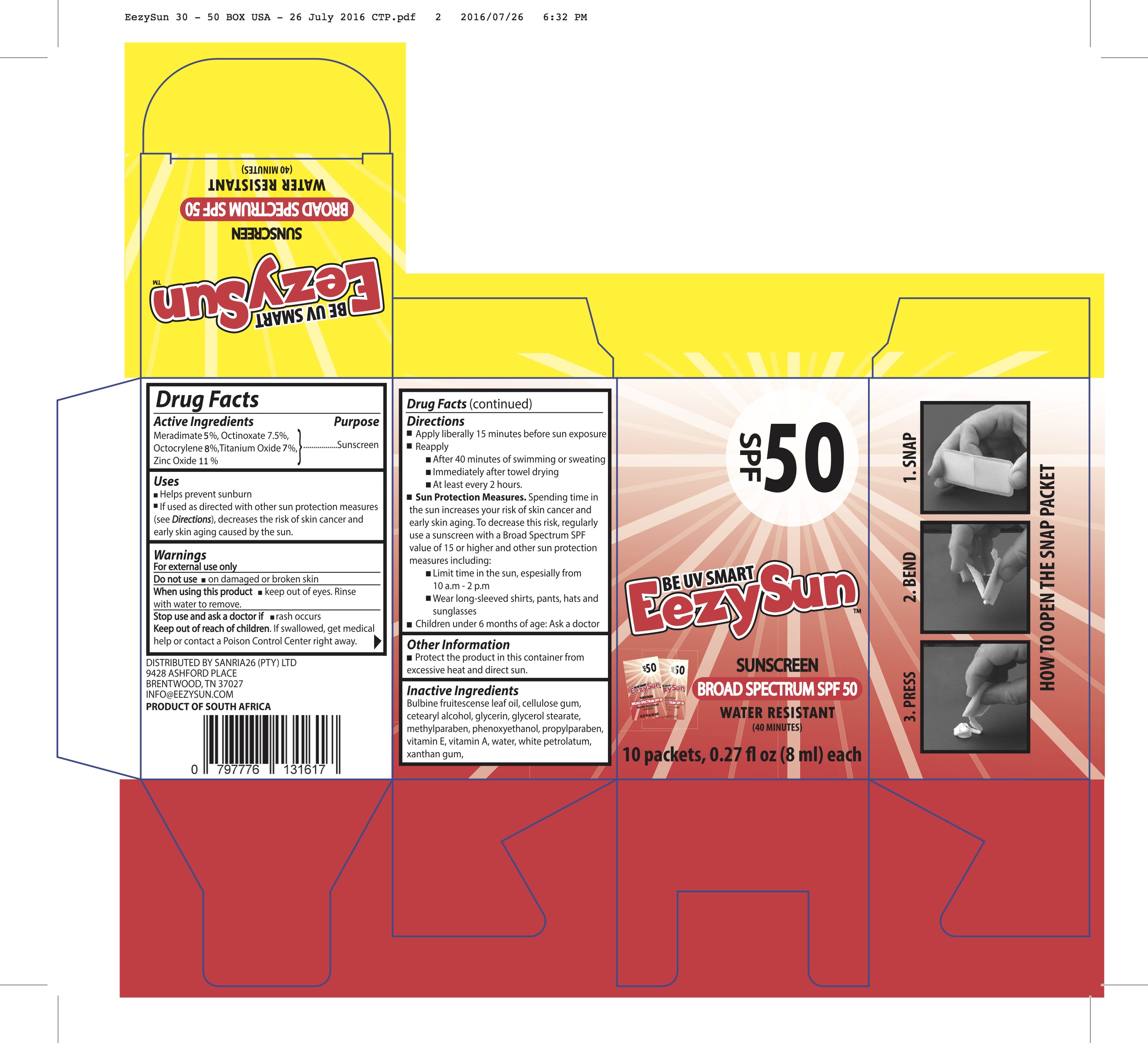 DRUG LABEL: Eezy Sun SPF 30
NDC: 70116-001 | Form: CREAM
Manufacturer: BIO EARTH MANUFACTURING (PTY) LTD
Category: otc | Type: HUMAN OTC DRUG LABEL
Date: 20171214

ACTIVE INGREDIENTS: MERADIMATE 30 mg/1 mL; OCTINOXATE 75 mg/1 mL; Octocrylene 40 mg/1 mL; TITANIUM DIOXIDE 50 mg/1 mL; Zinc Oxide 90 mg/1 mL
INACTIVE INGREDIENTS: BULBINE FRUTESCENS WHOLE; CARBOXYMETHYLCELLULOSE SODIUM, UNSPECIFIED FORM; CETOSTEARYL ALCOHOL; GLYCERIN; GLYCERYL MONOSTEARATE; METHYLPARABEN; PHENOXYETHANOL; PROPYLPARABEN; .ALPHA.-TOCOPHEROL; VITAMIN A; WATER; PETROLATUM; XANTHAN GUM

Eezy Sun

Actives

Meradimate, Octinoxate, Octocrylene, Titanium Dioxide, Zinc Oxide

Inactives

Bulbine Fruitescence leaf oil, Cellulose gum, Cetearyl alcohol, Glycerin, Glycerol Stearate, Methylparaben, Phenoxyethanol, Propylparaben, Vit E, Vit A, Water, White petrolatum, Xanthan gum

Dosage and Administration

Directions

Apply liberally 15 minutes before sun exposure Reapply

PLEASE RECYCLE

DISTRIBUTED BY SANRIA26 (PTY) LTD 9428 ASHFORD PLACE BRENTWOOD, TN 37027 INFO@EEZYSUN.COM PRODUCT OF SOUTH AFRICA

After 40 minutes of swimming or sweating Immediately after towel drying
At least every 2 hours.

Sun Protection Measures. Spending time in the sun increases your risk of skin cancer and early skin aging. To decrease this risk, regularly use a sunscreen with a Broad Spectrum SPF value of 15 or higher and other sun protection measures including:

Limit time in the sun, espesially from 10 a.m - 2 p.m

Wear long-sleeved shirts, pants, hats and sunglasses Children under 6 months of age: Ask a docto

Warnings

For external use only

Do not use : On Damaged on broken skin.

Stop use and ask a doctor if rash occurs
Keep out of reach of children. If swallowed, get medical help or contact a Poison Control Center right away.